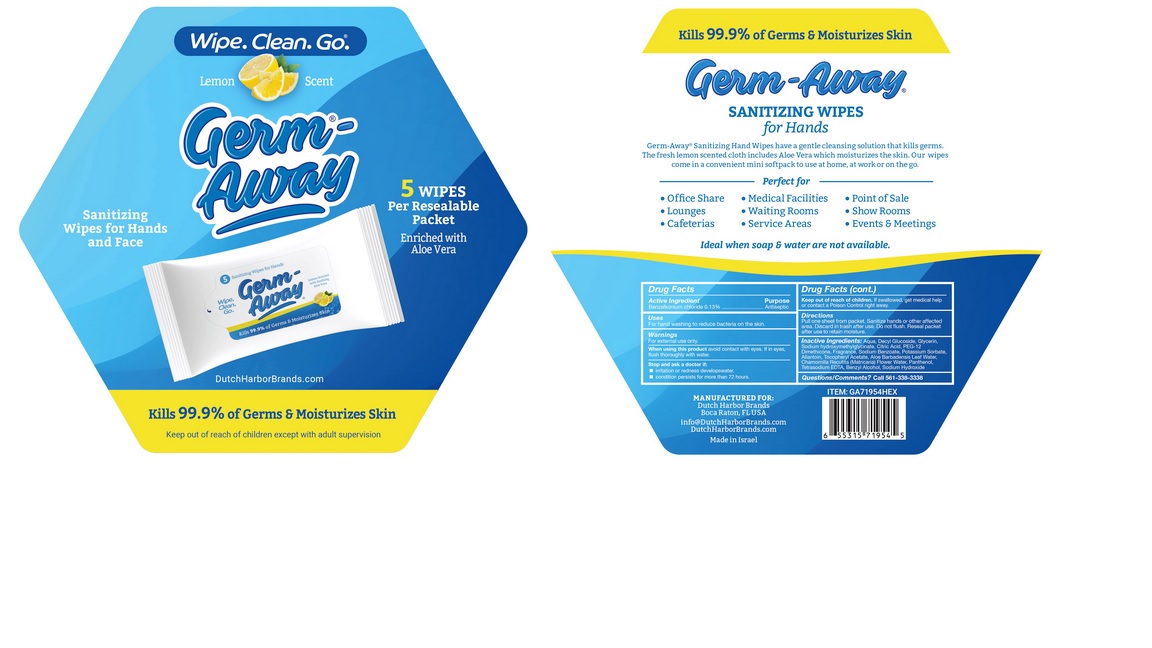 DRUG LABEL: Germ-Away
NDC: 74680-106 | Form: CLOTH
Manufacturer: Unico International Trading Corp
Category: otc | Type: HUMAN OTC DRUG LABEL
Date: 20200822

ACTIVE INGREDIENTS: BENZALKONIUM CHLORIDE 0.001 1/1 1
INACTIVE INGREDIENTS: WATER; SANDALORE; EDETATE SODIUM; PEG-12 DIMETHICONE (300 CST); SODIUM HYDROXYMETHYLGLYCINATE; POTASSIUM SORBATE; 4-TERT-BUTYLCYCLOHEXYL ACETATE; ANHYDROUS CITRIC ACID; PANTHENOL; 2-ISOBUTYL-4-METHYLTETRAHYDROPYRAN-4-OL; TETRAHYDROLINALOOL; 2,2'-OXYDIPROPANOL; ALLANTOIN; GLYCERIN; CHAMOMILE; DECYL GLUCOSIDE; SODIUM BENZOATE; ALOE VERA LEAF; EUCALYPTOL; .ALPHA.-TOCOPHEROL ACETATE; 3,7-DIMETHYL-1-OCTANOL; COUMARIN; DIPHENYL ETHER; CP FORMATE

Germ-Away

Active Ingredient

Benzalkonium chloride 01%

Purpose

Anti-bacterial

Keep out of the reach of children.

Keep out of reach of children, except with adult supervision.

Inactive Ingredients

Aqua, Decyl Glucoside, Glycerin, Sodium Hydroxymethylglycinate, Citric Acid, PEG-12 Dimethicone Copolyol, Tetrasodium EDTA, Potassium Sorbate, Sodium Benzoate, Aloe Barbadensis Leaf Extract, Chamomilla Recutita (Matricaria) Flower Extract, Allantoin, Panthenol, Tocopheryl Acetate, Fragrance

Warnings

For external use only. Do not use in the eyes.

Keep out of eyes. In case of eye contact, rinse with water. If irritation develops, discontinue use. Consult doctor if irritation persists for more than 72 hours.

If swallowed, seek medical attention or contact a Poison Control Center.

Directions

Pull one sheet from packet.

Use

Sanitize hands or other affected area. Discard in trash after use. Do not flush. Reseal packet after use to retain moisture.